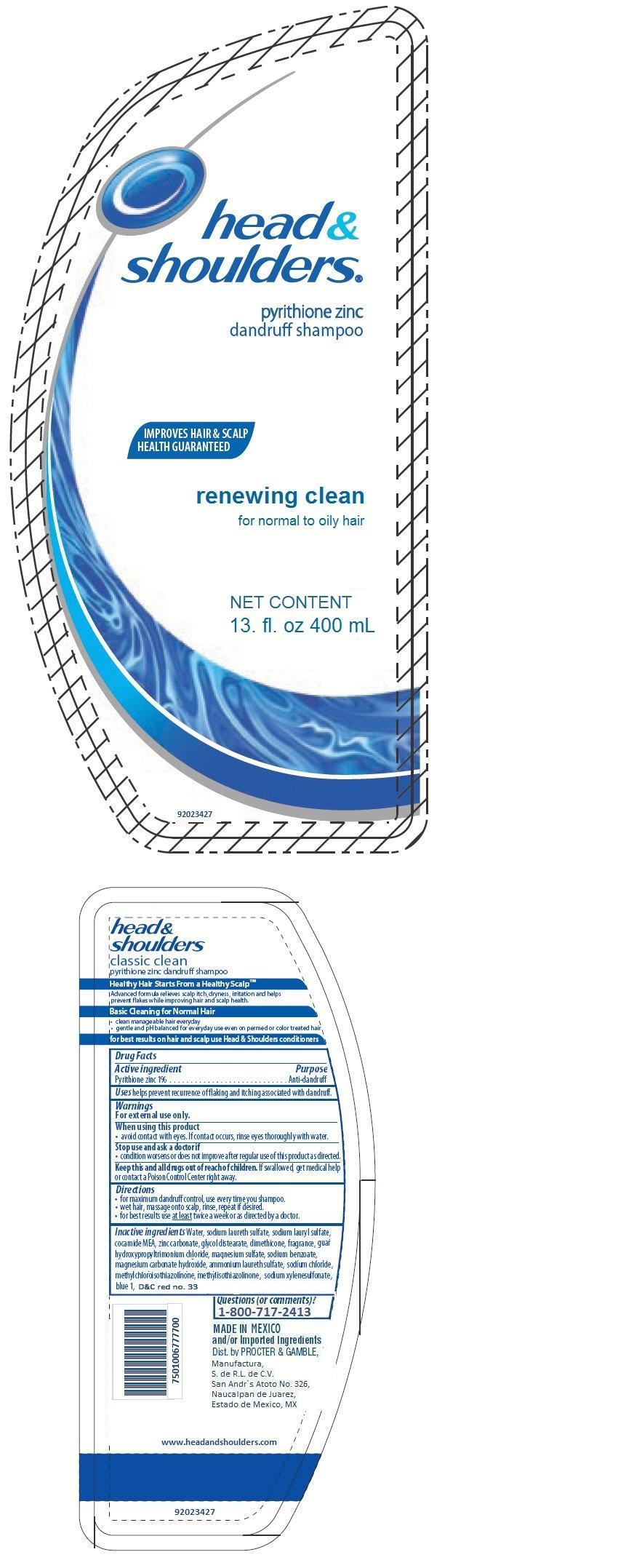 DRUG LABEL: Head and Shoulders
NDC: 51769-139 | Form: LOTION/SHAMPOO
Manufacturer: ALL NATURAL DYNAMICS
Category: otc | Type: HUMAN OTC DRUG LABEL
Date: 20130129

ACTIVE INGREDIENTS: Pyrithione Zinc 0.01 g/1 mL
INACTIVE INGREDIENTS: Water; sodium laureth sulfate; sodium lauryl sulfate; Coco Monoethanolamide; zinc carbonate; glycol distearate; dimethicone; guar hydroxypropyltrimonium chloride (1.7 substituents per saccharide); magnesium sulfate; sodium benzoate; magnesium carbonate hydroxide; sodium chloride; methylchloroisothiazolinone; methylisothiazolinone; sodium xylenesulfonate; FD&C blue no. 1; D&C RED NO. 33

Head and Shoulders renewing clean

Drug Facts

Active ingredient

Pyrithione zinc 1%

Purpose

Anti-dandruff

Uses

helps prevent recurrence of flaking and itching associated with dandruff.

Warnings

For external use only.

When using this product

- avoid contact with eyes. If contact occurs, rinse eyes thoroughly with water.

Stop use and ask a doctor if

- condition worsens or does not improve after regular use of this product as directed.

KEEP OUT OF REACH OF CHILDREN

Keep this and all drugs out of reach of children. If swallowed, get medical help or contact a Poison Control Center right away.

Directions

- for maximum dandruff control, use every time you shampoo.
- wet hair, massage onto scalp, rinse, repeat if desired.
- for best results use at least twice a week or as directed by a doctor.

Inactive ingredients

Water, sodium laureth sulfate, sodium lauryl sulfate, cocamide MEA, zinc carbonate, glycol distearate, dimethicone, fragrance, guar hydroxypropyltrimonium chloride, magnesium sulfate, sodium benzoate, magnesium carbonate hydroxide, ammonium laureth sulfate, sodium chloride, methylchloroisothiazolinone, methylisothiazolinone, sodium xylenesulfonate, blue 1, D&C red 33.

Questions (or comments)?

01-800-717-2413

Dist. by

Procter & Gamble Manufactura, S. de R.L. de C.V.

San Andr`s Atoto No. 326, Naucalpan de Juarez,

Estado de Mexico, MX

www.headandshoulders.com